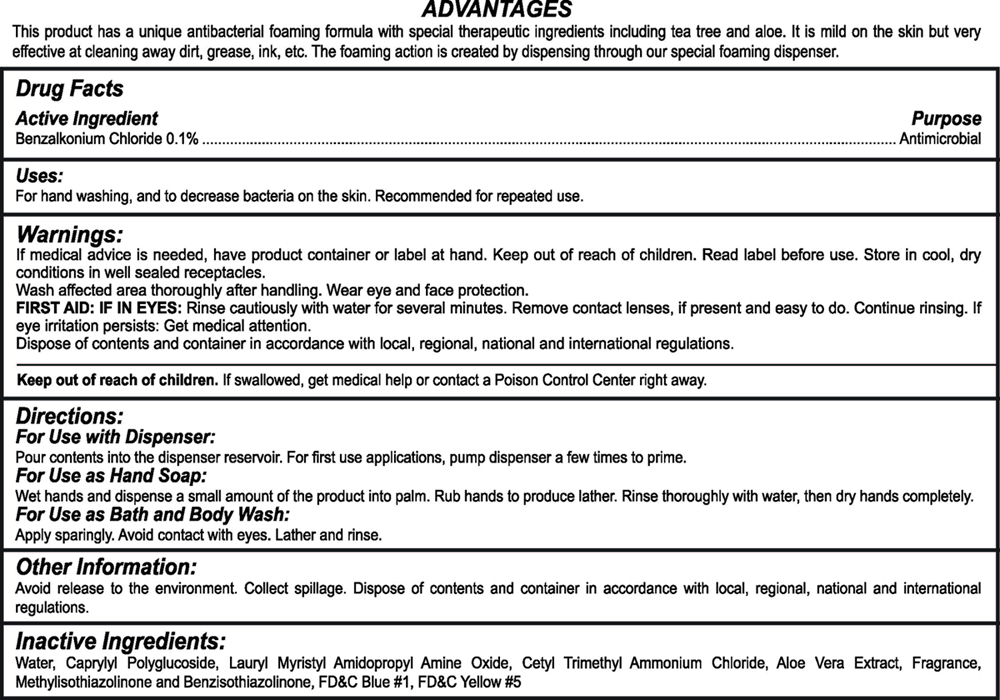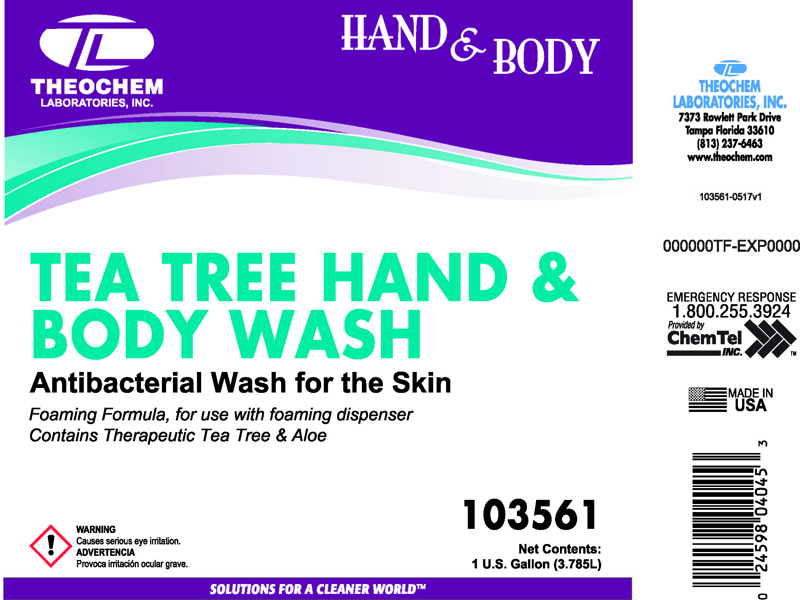 DRUG LABEL: Theochem Tea Tree Hand and Body Wash
NDC: 68878-561 | Form: SOAP
Manufacturer: Theochem Laboratories
Category: otc | Type: HUMAN OTC DRUG LABEL
Date: 20171115

ACTIVE INGREDIENTS: BENZALKONIUM CHLORIDE 0.1 mg/1 L
INACTIVE INGREDIENTS: WATER

TEA TREE HAND AND BODY WASH

Active Ingredient

Benzalkonium Chloride 0.1%

Purpose:

Antimicrobial

Uses:

For Hand Washing, and to decrease bacteria on the skin.

Recommended for repeated use.

Warnings:

If medical advice is needed, have product container or label at hand. Keep out of reach of children. Read label before use. Store in cool, dry conditions in well sealed receptacles.
Wash affected area thoroughly after handling. Wear eye and face protection.
FIRST AID: IF IN EYES: Rinse cautiously with water for several minutes. Remove contact lenses, if present and easy to do. Continue rinsing. If eye irritation persists: Get medical attention.
Dispose of contents and container in accordance with local, regional, national and international regulations.

Keep out of reach of children

If swallowed, get medical help or contact a Poison Control Center right away.

Directions:

For Use with Dispenser:
Pour contents into the dispenser reservoir. For first use applications, pump dispenser a few times to prime.
For Use as Hand Soap:
Wet hands and dispense a small amount of the product into palm. Rub hands to produce lather. Rinse thoroughly with water, then dry hands completely.
For Use as Bath and Body Wash:
Apply sparingly. Avoid contact with eyes. Lather and rinse.

Other Information

Avoid release to the environment. Collect spillage. Dispose of contents and container in accordance with local, regional, national and international regulations.

Inactive Ingredients:

Water, Caprylyl Polyglucoside, Lauryl Myristyl Amidopropyl Amine Oxide, Cetyl Trimethyl Ammonium Chloride, Aloe Vera Extract, Fragrance, Methylisothiazolinone and Benzisothiazolinone, FD&C Blue #1, FD&C Yellow #5

TEA TREE FRONT PANEL NET CONTENTS: 1 U.S GALLON

Tea Tree front.jpg